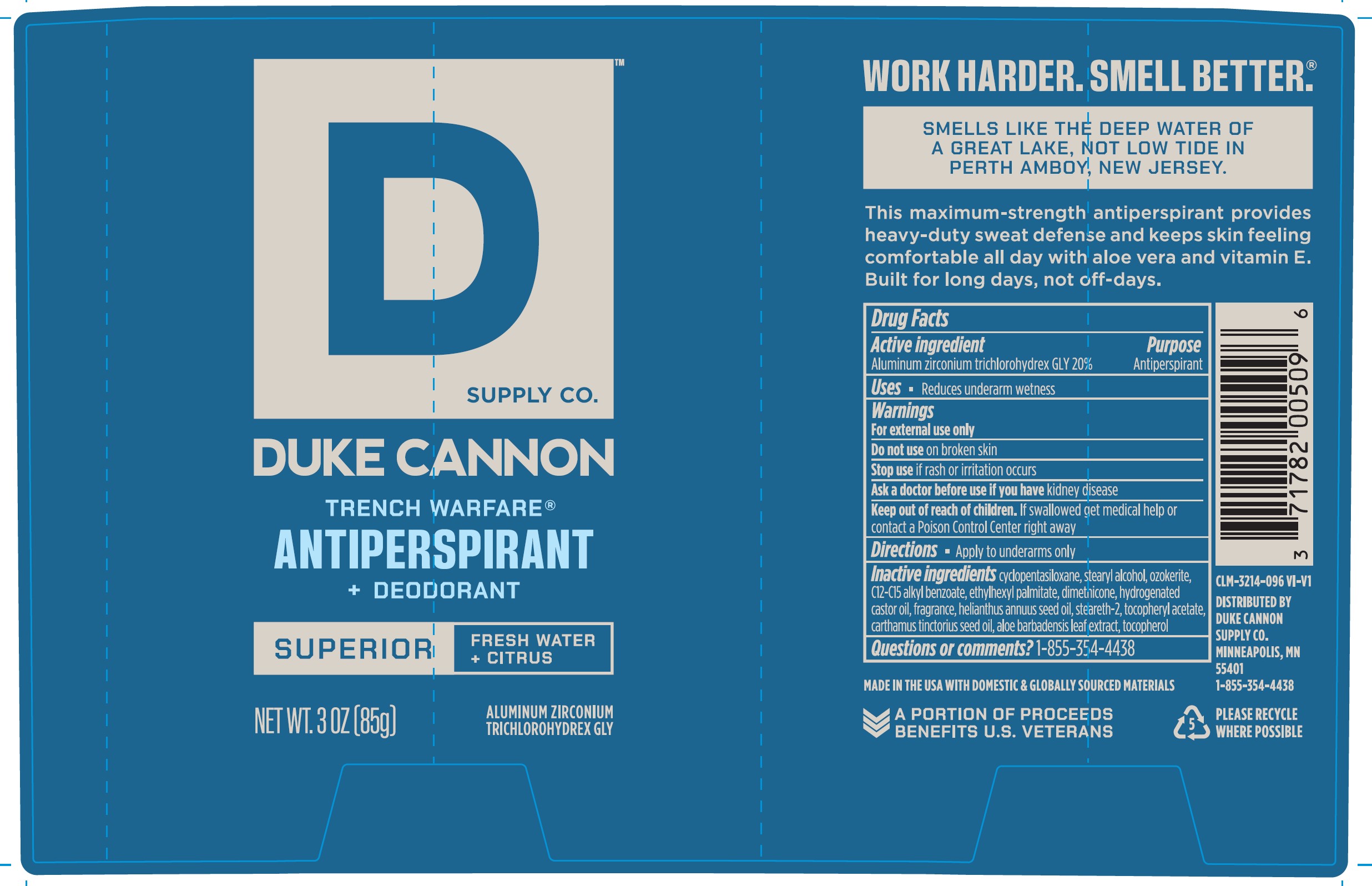 DRUG LABEL: Trench Warfare Antiperspirant Deodorant Superior
NDC: 71782-301 | Form: STICK
Manufacturer: Duke Cannon Supply Co.
Category: otc | Type: HUMAN OTC DRUG LABEL
Date: 20250101

ACTIVE INGREDIENTS: ALUMINUM ZIRCONIUM TRICHLOROHYDREX GLY 20 g/100 g
INACTIVE INGREDIENTS: STEARETH-2; ALOE VERA LEAF; CERESIN; ALKYL (C12-15) BENZOATE; DIMETHICONE; HYDROGENATED CASTOR OIL; ETHYLHEXYL PALMITATE; ALPHA-TOCOPHEROL ACETATE; CYCLOMETHICONE 5; STEARYL ALCOHOL; SUNFLOWER OIL; SAFFLOWER OIL

Trench Warfare Antiperspirant Deodorant Superior

Drug Facts

Active ingredient

Aluminum zirconium trichlorohydrex GLY 20%

Purpose

Antiperspirant

Uses

Reduces underarm wetness

Warnings

For external use only

Do not use

on broken skin

Stop use

if rash or irritation occurs

Ask a doctor before use

if you have kidney disease

Keep out of reach of children. If swallowed get medical help or contact a poison control center right away.

Directions

apply to underarms only

Inactive ingredients

cyclopentasiloxane, stearyl alcohol, ozokerite, C12-C15 alkyl benzoate, ethylhexyl palmitate, dimethicone, hydrogenated castor oil, fragrance, helianthus annuus seed oil, steareth-2, tocopheryl acetate, carthamus tinctorius seed oil, aloe barbadenis leaf extract, tocopherol

Questions or comments?

1-855-354-4438

Distributed by Duke Cannon Supply Co.

Minneapolis, MN 55401

Principal Display Panel

DUKE CANNON

Trench Warfare

Antiperspirant

+ Deodorant

Superior | Fresh Water + Citrus

Net Wt. 3 oz (85g)

Aluminum Zirconium Trichlorohydrex GLY